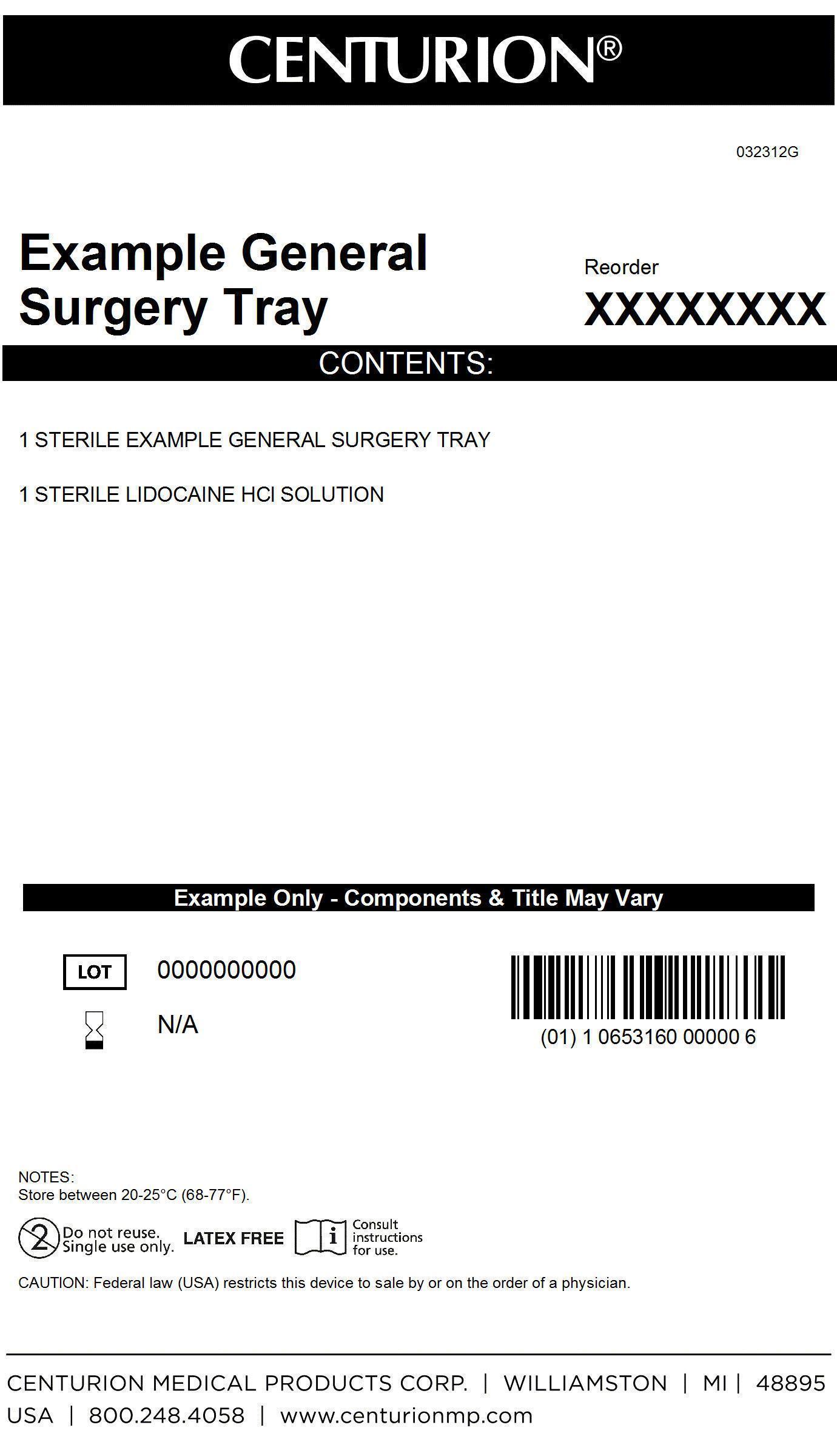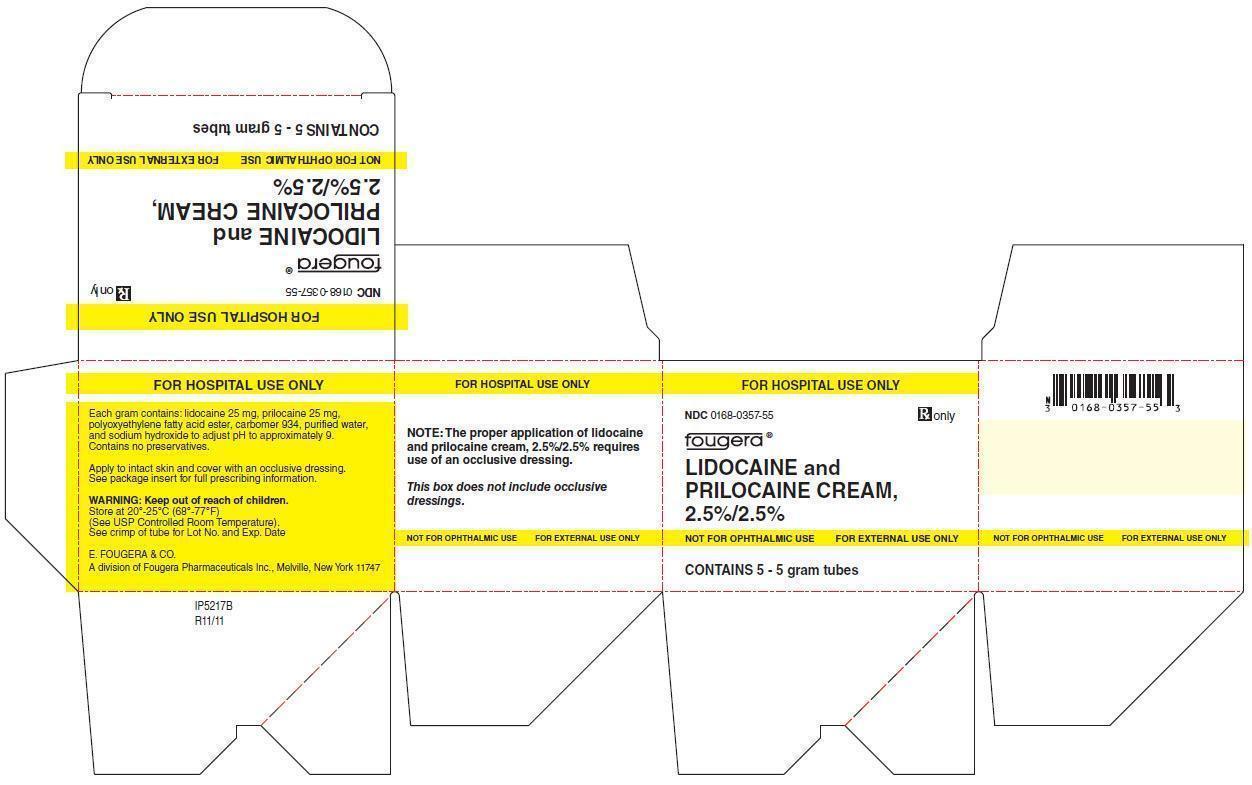 DRUG LABEL: General Surgery Tray
NDC: 24840-1521 | Form: KIT | Route: Topical
Manufacturer: Centurion Medical Products
Category: other | Type: MEDICAL DEVICE
Date: 20131002

ACTIVE INGREDIENTS: LIDOCAINE 25 mg/1 g; PRILOCAINE 25 mg/1 g
INACTIVE INGREDIENTS: CARBOMER HOMOPOLYMER TYPE B (ALLYL SUCROSE CROSSLINKED); SODIUM HYDROXIDE; Water

General Surgery Kit

Description

NOT FOR OPHTHALMIC USE
FOR EXTERNAL USE ONLY
Rx only